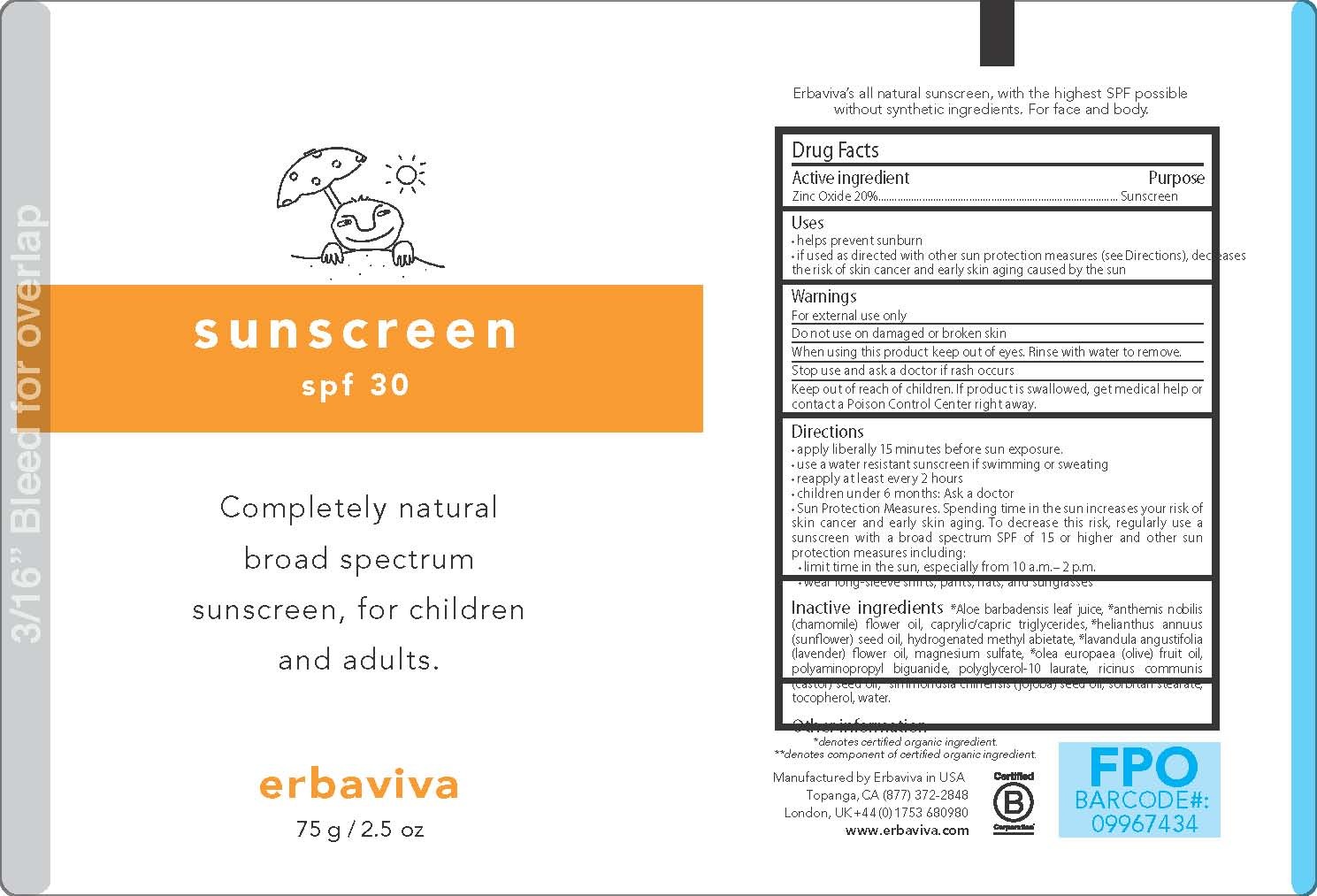 DRUG LABEL: SUNSCREEN
NDC: 43239-201 | Form: LOTION
Manufacturer: ERBAVIVA INC.
Category: otc | Type: HUMAN OTC DRUG LABEL
Date: 20120710

ACTIVE INGREDIENTS: ZINC OXIDE 20 g/100 g
INACTIVE INGREDIENTS: ALOE; CHAMAEMELUM NOBILE FLOWER OIL; MEDIUM-CHAIN TRIGLYCERIDES; SUNFLOWER OIL; LAVENDER OIL; MAGNESIUM SULFATE; OLIVE OIL; POLYAMINOPROPYL BIGUANIDE; POLYGLYCERYL-10 OLEATE; CASTOR OIL; JOJOBA OIL; SORBITAN MONOSTEARATE; TOCOPHEROL; WATER; GLYCERYL ABIETATE

SUNSCREEN

Active ingredient
ZINC OXIDE 20%

PURPOSE

SUNSCREEN

INDICATIONS AND USAGE

- HELPS PREVENT SUNBURN

WARNINGS

- FOR EXTERNAL USE ONLY

- DO NOT USE ON DAMAGED OR BROKEN SKIN.

WHEN USING

- KEEP OUT OF EYES. RINSE WITH WATER TO REMOVE.

STOP USE

- AND ASK A DOCTOR IF RASH OCCURS.

Keep out of reach of children. If product is swallowed, get medical help or contact a Poison Control Center right away.

Directions
• apply liberally 15 minutes before sun exposure.
• use a water resistant sunscreen if swimming or sweating
• reapply at least every 2 hours

OTHER SAFETY INFORMATION

- Sun Protection Measures. Spending time in the sun increases your risk of skin cancer and early skin aging. To decrease this risk, regularly use a sunscreen with a broad spectrum SPF of 15 or higher and other sun protection measures including:
-
  - limit time in the sun, especially from 10 a.m.–2 p.m.
  - wear long-sleeve shirts, pants, hats, and sunglasses

PEDIATRIC USE

- CHILDREN UNDER 6 MONTHS OF AGE: ASK A DOCTOR

INACTIVE INGREDIENT

Inactive ingredients: *Aloe barbadensis leaf juice, *anthemis nobilis (chamomile) flower oil, caprylic/capric triglycerides, *helianthus annuus (sunflower) seed oil, hydrogenated methyl abietate, *lavandula angustifolia (lavender) flower oil, magnesium sulfate, *olea europaea (olive) fruit oil, polyaminopropyl biguanide, polyglycerol-10 laurate, ricinus communis (castor) seed oil, *simmondsia chinensis (jojoba) seed oil, sorbitan stearate, tocopherol, water.

OTHER INFORMATION

- PROTECT THE PRODUCT IN THIS CONTAINER FROM EXCESSIVE HEAT AND DIRECT SUN.

PACKAGE LABEL

ERBAVIVA
SUNSCREEN
SPF30
Completely natural broad spectrum
sunscreen, for children and adults.